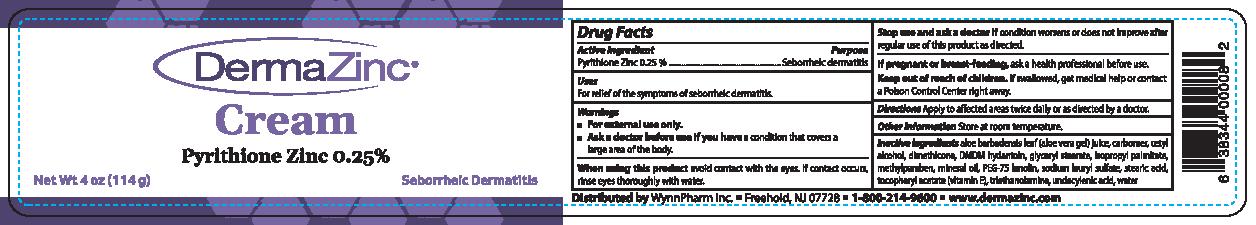 DRUG LABEL: DermaZinc
NDC: 35324-001 | Form: CREAM
Manufacturer: WynnPharm Inc
Category: otc | Type: HUMAN OTC DRUG LABEL
Date: 20251114

ACTIVE INGREDIENTS: PYRITHIONE ZINC 0.25 g/100 g
INACTIVE INGREDIENTS: .ALPHA.-TOCOPHEROL ACETATE; PEG-75 LANOLIN; ALOE VERA LEAF; CARBOMER 980; CETYL ALCOHOL; DIMETHICONE 200; GLYCERYL STEARATE SE; STEARIC ACID; METHYLPARABEN; DMDM HYDANTOIN; MINERAL OIL; WATER; ISOPROPYL PALMITATE; TROLAMINE; UNDECYLENIC ACID

DermaZinc Cream

ACTIVE INGREDIENT

Pyrithione Zinc 0.25%

Keep Out of Reach of Children.

PURPOSE

Seborrheic Dermatitis treatment

DOSAGE AND ADMINISTRATION

Apply to affected area twice daily or as directed by a doctor.

INDICATIONS AND USAGE

For relief of the symptoms of seborrheic dermatitis.

Warnings
■ For external use only.
■ Ask a doctor before use if you have a condition that covers a large area of the body.

When using this product avoid contact with the eyes. If contact occurs, rinse eyes thoroughly with
water.
Stop use and ask a doctor if condition worsens or does not improve after regular use of this
product as directed.

If pregnant or breast-feeding, ask a health professional before use. Keep out of reach of children.
If swallowed, get medical help or contact a Poison Control Center right away.

INACTIVE INGREDIENT

Inactive ingredients aloe barbadensis leaf (aloe vera gel) juice, carbomer, cetyl
alcohol, dimethicone, DMDM hydantoin, glyceryl stearate, isopropyl palmitate, methylparaben,
mineral oil, PEG-75 lanolin, sodium 1auryl sulfate, stearic acid, tocopheryl acetate (vitamin E),
triethanolamine,undecylenic acid, water